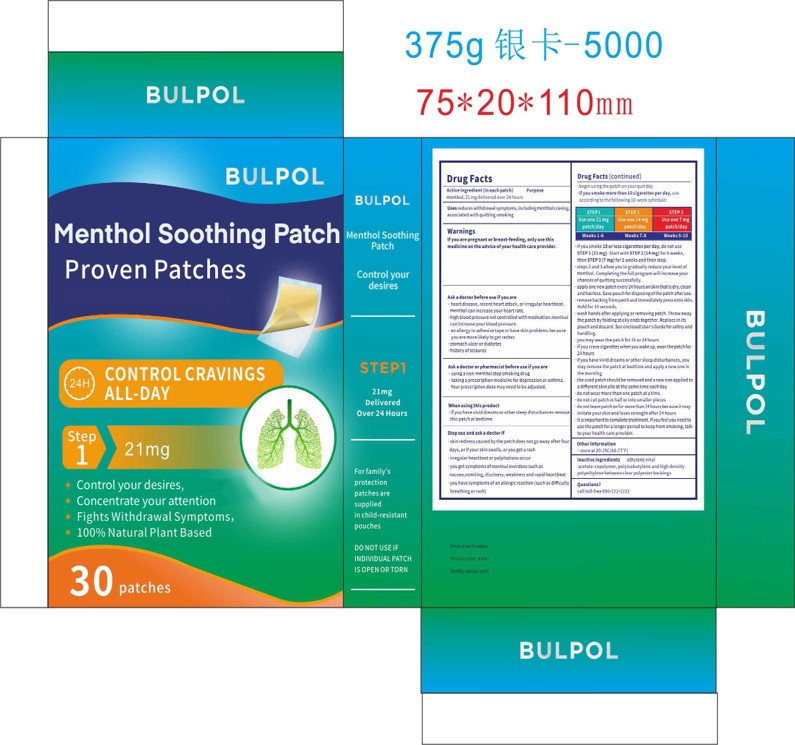 DRUG LABEL: BULPOL Smoking Patches
NDC: 84867-017 | Form: LIQUID
Manufacturer: Jiashen International Trade Limited
Category: otc | Type: HUMAN OTC DRUG LABEL
Date: 20250717

ACTIVE INGREDIENTS: MENTHOL 21 mg/1 g
INACTIVE INGREDIENTS: ETHYLENE-VINYL ACETATE COPOLYMER (19% VINYLACETATE); PETROSELINIC ACID

ACTIVE INGREDIENT

menthol

PURPOSE

Stop smoking aid

WHEN USING

reduces withdrawal symptoms, including nicotine craving, associated with quitting smoking

WARNINGS

If you are pregnant or breast-feeding, only use this medicine on the advice of your healthcare provider.Smoking can seriously harm your child.Try to stop smoking without using any nicotine replacement medicine.This medicine is believed to safer than smoking.However, the risks to your child from this medicine are not full known.

Ask a doctor or pharmacist before use ifyou are"usinga non-nicotine stop smoking drugtaking a prescription medicine for depression or asthma.Your prescription dose may need to be adjusted.

Keep out of reach of children and pets.
Used patches have enough nicotine to poison children and pets.If swallowed, get medical help or contact a Poison Control Center right away.Save pouch to use for patch di posal.Dispose of the used patches by folding sticky ends together and putting in pouch.

INDICATIONS AND USAGE

ifyou smoke 10 orless cigarettes per day, do not useSTEP 1 (21 mg). Start with STEP 2 (14 mg) for 6 weeks,then STEP 3 (7 mg) for 2 weeks and then stop.steps 2 and 3 allow you to gradually reduce yourlevel ofnicotine.Completingthe full program willincrease yourchances ofquittingsuccessfully.apply one new patch every 24 hours on skin that is dry, cleanand hairless. Save pouch for disposingofthe patch after use.remove backingfrom patch andimmediately press onto skin.Hold for 10 seconds.

DOSAGE AND ADMINISTRATION

STEP1
Use one 21 mgpatch/day
Weeks 1-6
STEP 2
Use one 14 mg
patch/day
Weeks 7-8
STEP 3
Use one7mg
patch/day
Weeks9-10

INACTIVE INGREDIENT

nactive ingredientsethylene vinylacetate-copolymer, polyisobutylene and high densitypolyethylene between clearpolyester backings